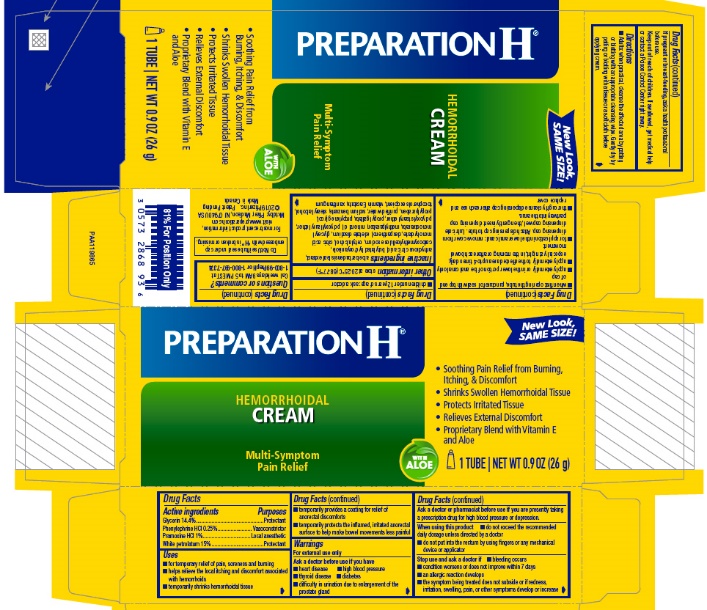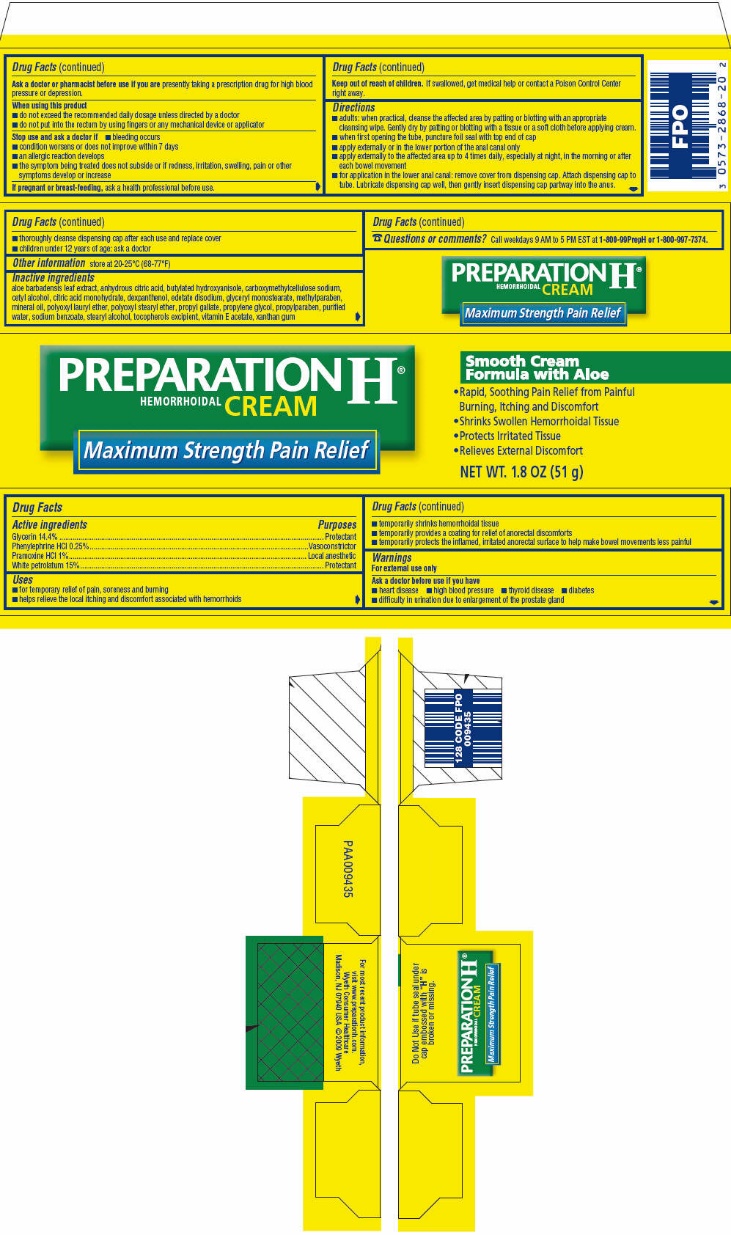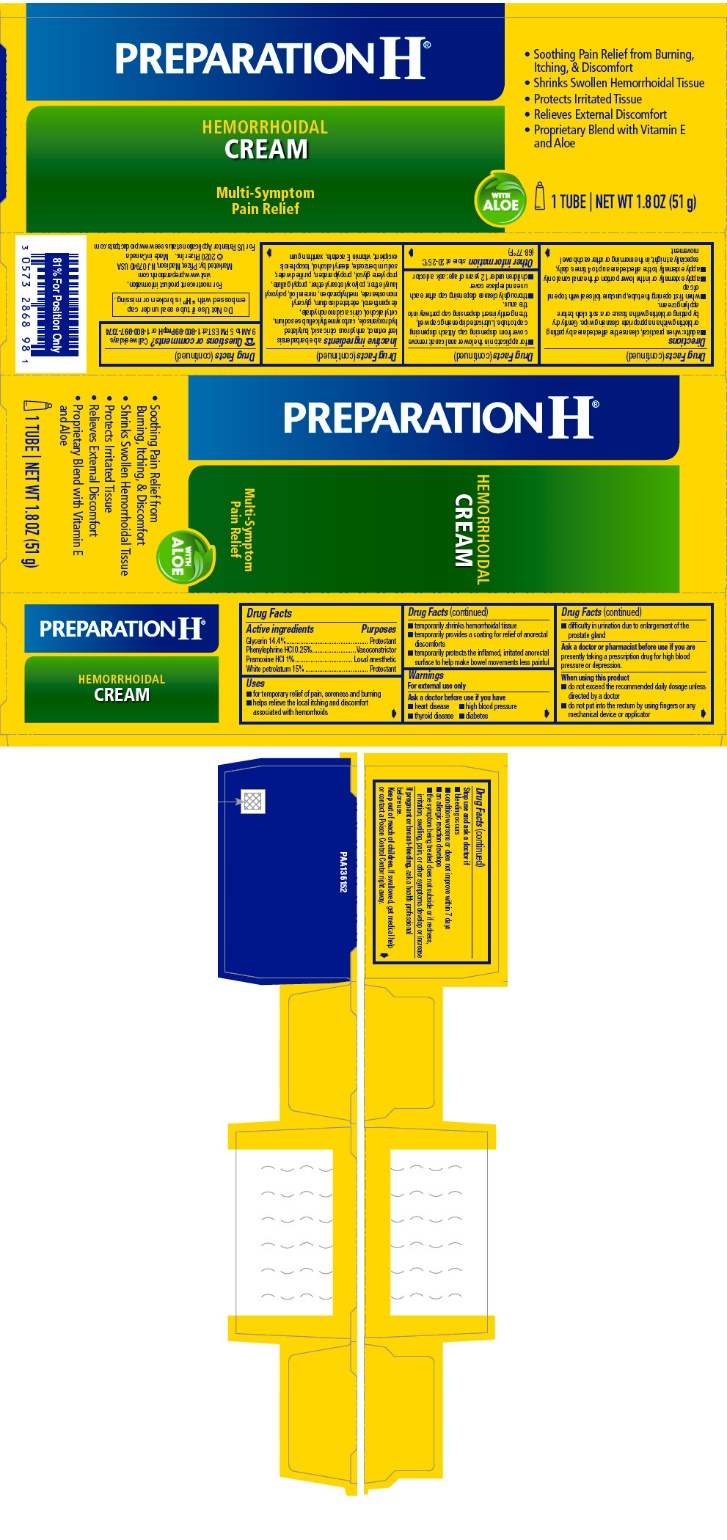 DRUG LABEL: PREPARATION H

NDC: 0573-2868 | Form: CREAM
Manufacturer: Haleon US Holdings LLC
Category: otc | Type: HUMAN OTC DRUG LABEL
Date: 20240405

ACTIVE INGREDIENTS: GLYCERIN 144 mg/1 g; PHENYLEPHRINE HYDROCHLORIDE 2.5 mg/1 g; PRAMOXINE HYDROCHLORIDE 10 mg/1 g; PETROLATUM 150 mg/1 g
INACTIVE INGREDIENTS: ALOE VERA LEAF; .ALPHA.-TOCOPHEROL ACETATE; ANHYDROUS CITRIC ACID; BUTYLATED HYDROXYANISOLE; CARBOXYMETHYLCELLULOSE SODIUM, UNSPECIFIED; CETYL ALCOHOL; CITRIC ACID MONOHYDRATE; DEXPANTHENOL; EDETATE DISODIUM; GLYCERYL MONOSTEARATE; LAURETH-23; METHYLPARABEN; MINERAL OIL; PROPYL GALLATE; PROPYLENE GLYCOL; PROPYLPARABEN; SODIUM BENZOATE; STEARYL ALCOHOL; WATER; XANTHAN GUM

PREPARATION H®

Drug Facts

ACTIVE INGREDIENT

PURPOSE

Active ingredients | Purposes
Glycerin 14.4% | Protectant
Phenylephrine HCl 0.25% | Vasoconstrictor
Pramoxine HCl 1% | Local anesthetic
White petrolatum 15% | Protectant

Uses

- for temporary relief of pain, soreness and burning
- helps relieve the local itching and discomfort associated with hemorrhoids
- temporarily shrinks hemorrhoidal tissue
- temporarily provides a coating for relief of anorectal discomforts
- temporarily protects the inflamed, irritated anorectal surface to help make bowel movements less painful

Warnings

For external use only

Ask a doctor before use if you have

- heart disease
- high blood pressure
- thyroid disease
- diabetes
- difficulty in urination due to enlargement of the prostate gland

Ask a doctor or pharmacist before use if you arepresently taking a prescription drug for high blood pressure or depression.

When using this product

- do not exceed the recommended daily dosage unless directed by a doctor
- do not put into the rectum by using fingers or any mechanical device or applicator

Stop use and ask a doctor if

- bleeding occurs
- condition worsens or does not improve within 7 days
- an allergic reaction develops
- the symptom being treated does not subside or if redness, irritation, swelling, pain, or other symptoms develop or increase

PREGNANCY OR BREAST FEEDING

If pregnant or breast-feeding,ask a health professional before use.

Keep out of reach of children.If swallowed, get medical help or contact a Poison Control Center right away.

Directions

- Adults: when practical, cleanse the affected area by patting or blotting with an appropriate cleansing wipe. Gently dry by patting or blotting with a tissue or a soft cloth before applying cream.
- when first opening the tube, puncture foil seal with top end of cap
- apply externally or in the lower portion of the anal canal only
- apply externally to the affected area up to 4 times daily, especially at night, in the morning or after each bowel movement
- for application in the lower anal canal: remove cover from dispensing cap. Attach dispensing cap to tube. Lubricate dispensing cap well, then gently insert dispensing cap partway into the anus.
- thoroughly cleanse dispensing cap after each use and replace cover
- children under 12 years of age: ask a doctor

Other information

store at 20-25°C (68-77°F)

Inactive ingredients

aloe barbadensis leaf extract, anhydrous citric acid, butylated hydroxyanisole, carboxymethylcellulose sodium, cetyl alcohol, citric acid monohydrate, dexpanthenol, edetate disodium, glyceryl monostearate, methylparaben, mineral oil, polyoxyl lauryl ether, polyoxyl stearyl ether, propyl gallate, propylene glycol, propylparaben, purified water, sodium benzoate, stearyl alcohol, tocopherols excipient, vitamin E acetate, xanthan gum

Questions or comments?

Call weekdays 9 AM to 5 PM EST at 1-800-99PrepH or 1-800-997-7374

PRINCIPAL DISPLAY PANEL - 26 g Tube Carton

PREPARATION H®

HEMORRHOIDAL
CREAM

Multi-Symptom
Pain Relief

WITH
ALOE

New Look,
SAME SIZE!

- Soothing Pain Relief from Burning,
  Itching, & Discomfort
- Shrinks Swollen Hemorrhoidal Tissue
- Protects Irritated Tissue
- Relieves External Discomfort
- Proprietary Blend with Vitamin E
  and Aloe

1 TUBE | NET WT 0.9 OZ (26 g)

PRINCIPAL DISPLAY PANEL - 51 g Tube Carton

PREPARATION H®
HEMORRHOIDAL CREAM

Maximum Strength Pain Relief

Smooth Cream
Formula with Aloe

1. Rapid, Soothing Pain Relief from Painful
  Burning, Itching and Discomfort
2. Shrinks Swollen Hemorrhoidal Tissue
3. Protects Irritated Tissue
4. Relieves External Discomfort

NET WT. 1.8 OZ (51 g)

PRINCIPAL DISPLAY PANEL - 51 g Tube Carton - NDC 0573-2868-98

PREPARATION H®

HEMORRHOIDAL
CREAM

Multi-Symptom
Pain Relief

WITH
ALOE

- Soothing Pain Relief from Burning,
  Itching, & Discomfort
- Shrinks Swollen Hemorrhoidal Tissue
- Protects Irritated Tissue
- Relieves External Discomfort
- Proprietary Blend with Vitamin E
  and Aloe

1 TUBE | NET WT 1.8 OZ (51 g)